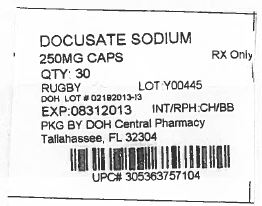 DRUG LABEL: EXTRA STRENGTH STOOL SOFTENER LAXATIVE
NDC: 53808-0902 | Form: CAPSULE, LIQUID FILLED
Manufacturer: State of Florida DOH Central Pharmacy
Category: otc | Type: HUMAN OTC DRUG LABEL
Date: 20140303

ACTIVE INGREDIENTS: DOCUSATE SODIUM 250 mg/1 1
INACTIVE INGREDIENTS: FD&C RED NO. 40; FD&C YELLOW NO. 6; GELATIN; GLYCERIN; POLYETHYLENE GLYCOLS; PROPYLENE GLYCOL; WATER; SORBITOL

Drug Facts

Active Ingredient (in each softgel)

Docusate Sodium 250 mg

Purpose

Stool softener

Uses

- for the prevention of dry, hard stools
- for relief of occasional constipation
- this product generally produces a bowel movement within 12 to 72 hours

Warnings

Do not use

- if you are currently taking mineral oil, unless directed by a doctor
- when abdominal pain, nausea, or vomiting are present
- for more than 1 week, unless directed by a doctor

Ask a doctor before use if

you notice a sudden change in bowel habits that persists over a period of 2 weeks.

Stop use and ask a doctor if

- you have rectal bleeding
- you fail to have a bowel movement after use

These could be signs of a serious condition.

If pregnant or breast-feeding,

ask a health professional before use.

Keep out of reach of children.

In case of overdose, get medical help or contact a Poison Control Center right away.

Directions

- adults and children 12 years of age and over: take1 softgel daily or as directed by a doctor
- children under 12 years of age: take as directed by a doctor

Other information

- each softgel contains: sodium 15 mg
- store between 15º-30ºC (59º-86ºF)

Inactive Ingredients

edible white ink, FD&C red #40, FD&C yellow #6, gelatin, glycerin, polyethylene glycol, propylene glycol, purified water, sorbitol special

Questions or comments?

1-800-645-2158

Distributed by: Rugby Laboratories
31778 Enterprise Drive
Livonia, MI 48150
www.rugbylaboratories.com

This Product was Repackaged By:

State of Florida DOH Central Pharmacy
104-2 Hamilton Park Drive
Tallahassee, FL 32304
USA

And supplied by State of Florida DOH Central Pharmacy as follows:

NDC | Strength | Quantity/Form | Color | Source Prod. Code
53808-0902-1 | 250 MG | 30 Capsules in a Blister Pack | orange | 0536-3757

PACKAGE LABEL

Label Image for 53808-0902
250mg